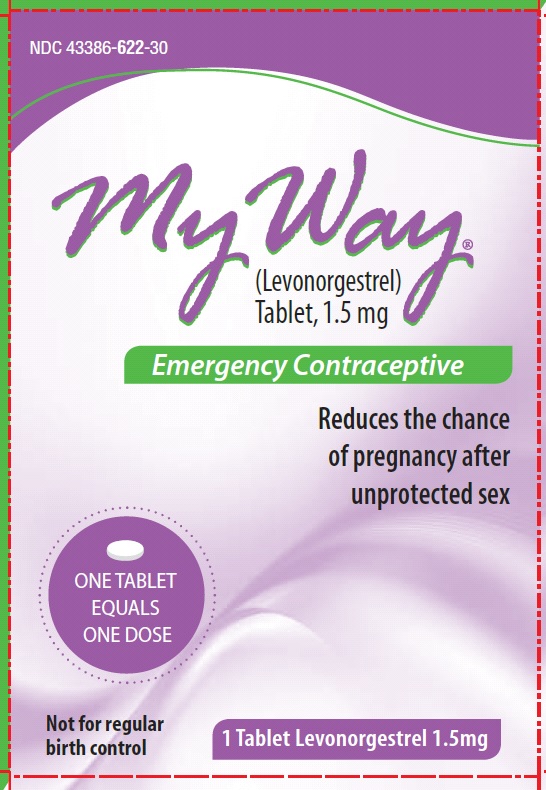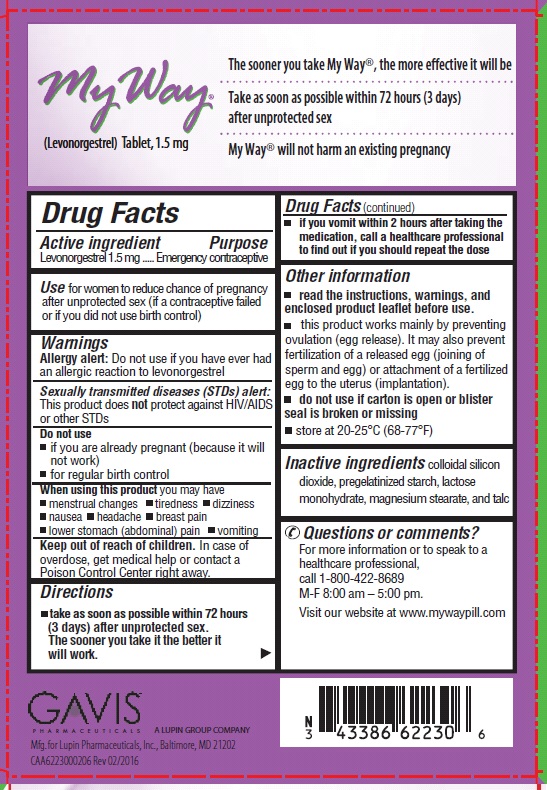 DRUG LABEL: My Way
NDC: 43386-622 | Form: TABLET
Manufacturer: Lupin Pharmaceuticals,Inc.
Category: otc | Type: HUMAN OTC DRUG LABEL
Date: 20160617

ACTIVE INGREDIENTS: LEVONORGESTREL 1.5 mg/1 1
INACTIVE INGREDIENTS: SILICON DIOXIDE; STARCH, CORN; LACTOSE MONOHYDRATE; MAGNESIUM STEARATE; TALC

Drug Facts

Active Ingredient

Levonorgestrel 1.5mg

Purpose

Emergency contraceptive

Indications

Use for women to reduce chance of pregnancy after unprotected sex (if a contraceptive failed or if you did not use birth control)

Warnings

Allergy alert: Do not use if you have ever had an allergic reaction to Levonorgestrel

Sexually transmitted diseases (STDs) alert: This product does not protect against HIV/AIDS or other STDs

Do not use

- if you are already pregnant (because it will not work)
- for regular birth control

When using this product you may have

- menstrual changes
- nausea
- lower stomach (abdominal) pain
- tiredness
- headache
- dizziness
- breast pain
- vomiting

Keep out of reach of children

In case of overdose, get medical help or contact a Poison Control Center right away.

Directions

- take as soon as possible within 72 hours (3 days) after unprotected sex. The sooner you take it the better it will work.
- if you vomit within 2 hours after taking the medication, call a healthcare professional to find out if you should repeat the dose

Other Information

- read the instructions, warnings and enclosed product leaflet before use
- this product works mainly by preventing ovulation (egg release). It may also prevent fertilization of a released egg (joining of sperm and egg) or attachment of a fertilized egg to the uterus (implantation).
- do not use if carton is open or blister seal is broken or missing
- store at 20-25°C (68-77°F)

Inactive ingredients

colloidal silicon dioxide, pregelatinized starch, lactose monohydrate, magnesium stearate and talc

Questions?

For more information or to speak to a healthcare professional, call 1-800-422-8689 or visit our website at www.mywaypill.com

My Way

Emergency Contraceptive

What You Need to Know

What is My Way?

My Way is emergency contraception that helps prevent pregnancy after birth control failure or unprotected sex. It is a backup method of preventing pregnancy and should not be used as regular birth control.

What My Way is not.

My Way will not work if you are already pregnant and will not affect an existing pregnancy. My Way will not protect you from HIV infection (the virus that causes AIDS) and other sexually transmitted diseases (STDs).

When should I use My Way?

The sooner you take emergency contraception, the better it works. You should use My Way within 72 hours (3 days) after you have had unprotected sex.

My Way is a backup or emergency method of birth control you can use when:

- Your regular birth control was used incorrectly or failed
- You did not use any birth control method

When not to use My Way.

My Way should not be used:

- as a regular birth control method, because it's not as effective as regular birth control.
- if you are already pregnant, because it will not work.
- if you are allergic to levonorgestrel or any other ingredients in My Way .

How does My Way work?

My Way is one tablet with levonorgestrel, a hormone that has been used in many birth control pills for several decades. My Way contains a higher dose of levonorgestrel than birth control pills, but works in a similar way to prevent pregnancy. It works mainly by stopping the release of an egg from the ovary. It is possible that My Way may also work by preventing fertilization of an egg (the uniting of sperm with the egg) or by preventing attachment (implantation) to the uterus (womb).

How can I get the best results from My Way?

You have 72 hours (3 days) to try to prevent pregnancy after birth control failure or unprotected sex. The sooner you take My Way, the better it works.

How effective is My Way?

If My Way is taken as directed, it can significantly decrease the chance that you will get pregnant. About 7 out of every 8 women who would have gotten pregnant will not become pregnant.

How will I know My Way worked?

You will know My Way has been effective when you get your next period, which should come at the expected time, or within a week of the expected time. If your period is delayed beyond 1 week, it is possible you may be pregnant. You should get a pregnancy test and follow up with your healthcare professional.

Will I experience any side effects?

- some women may have changes in their period, such as a period that is heavier or lighter or a period that is early or late. If your period is more than a week late, you may be pregnant.

- if you have severe abdominal pain, you may have an ectopic pregnancy, and should get immediate medical attention.
- when used as directed, My Way is safe and effective. Side effects may include changes in your period, nausea, lower stomach (abdominal) pain, tiredness, headache, dizziness, and breast tenderness.
- if you vomit within 2 hours of taking the medication, call a healthcare professional to find out if you should repeat the dose.

What if I still have questions about My Way?

If you have questions or need more information, call 1-800-422-8689, or visit our website at www.mywaypill.com

Other Information

Keep out of reach of children:

In case of overdose, get medical help or contact a Poison Control Center right away at 1-800-222-1222.

Do not use if the blister seal is opened.

Store at room temperature 20–25°C (68–77°F).

Active ingredient: levonorgestrel 1.5 mg

Inactive ingredients: colloidal silicon dioxide, pregelatinized starch, lactose monohydrate, magnesium stearate, and talc

If you are sexually active, you should see a healthcare provider for routine checkups. Your healthcare provider will talk to you about and, if necessary, test you for sexually transmitted diseases, teach you about effective methods of routine birth control, and answer any other questions you may have.

Manufactured by:

Novel Laboratories, Inc.

Somerset, NJ 08873

PI6223000201

Rev. 02/2014

PRINCIPAL DISPLAY PANEL

My Way (levonorgestrel) Tablet , 1.5 mg

NDC 43386-622-30

emergency contraceptive

Reduces chance of pregnancy after unprotected sex.

Not for regular birth control.

Contains 1 Tablet 1.5mg

Front Panel

Back Panel